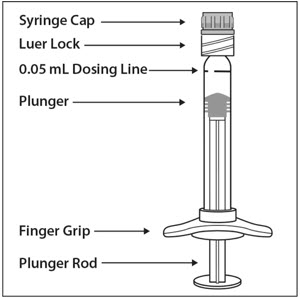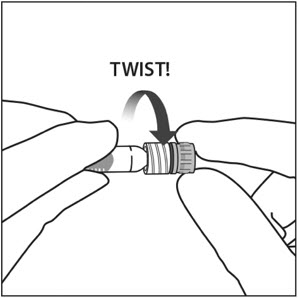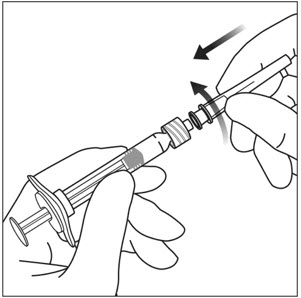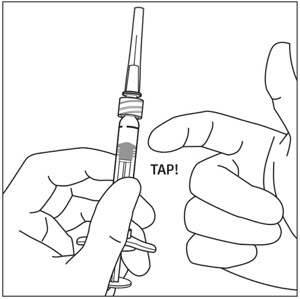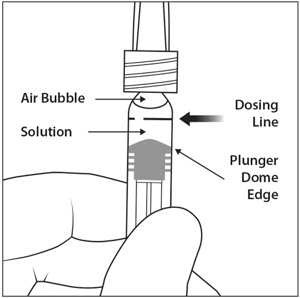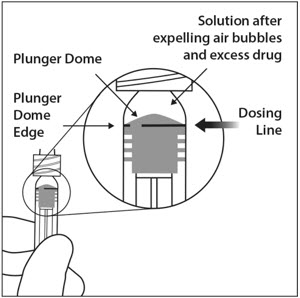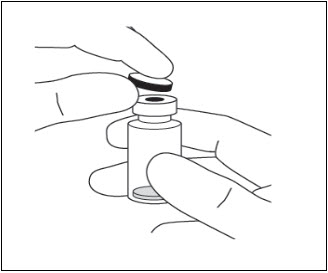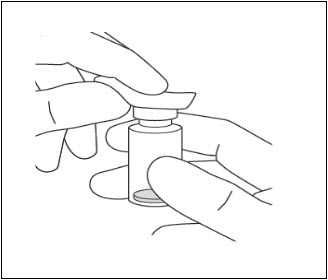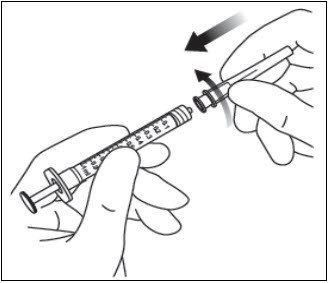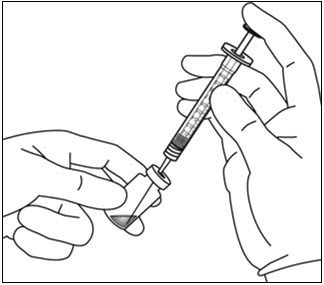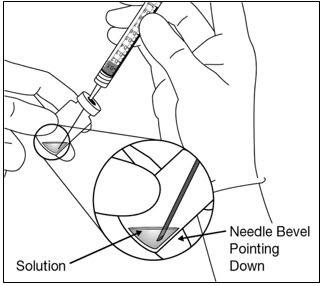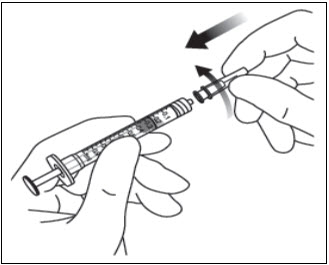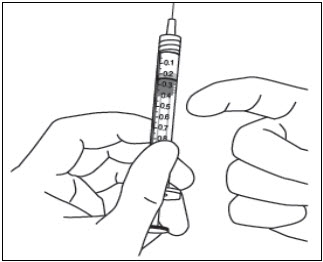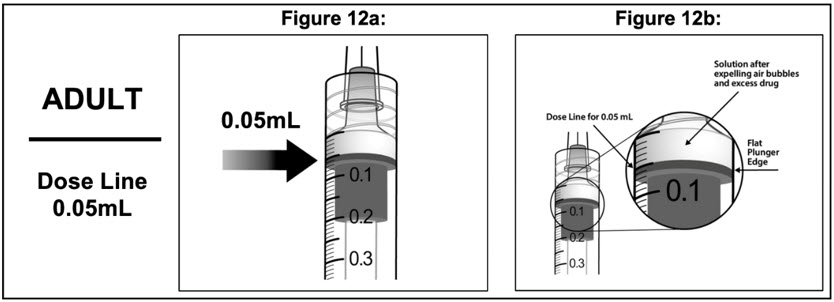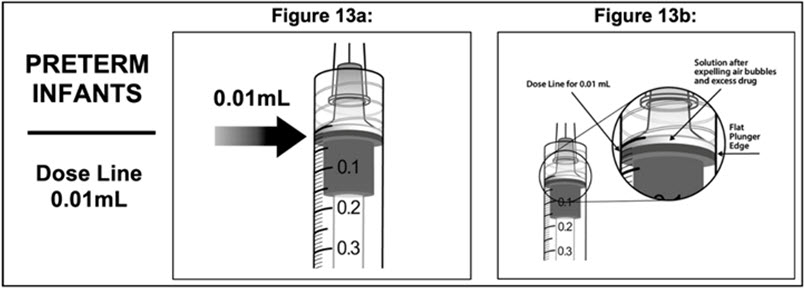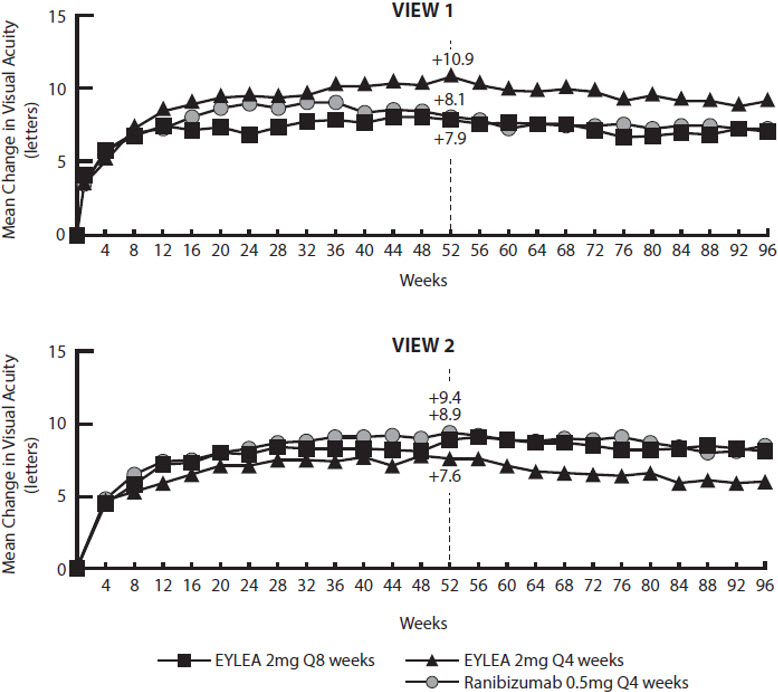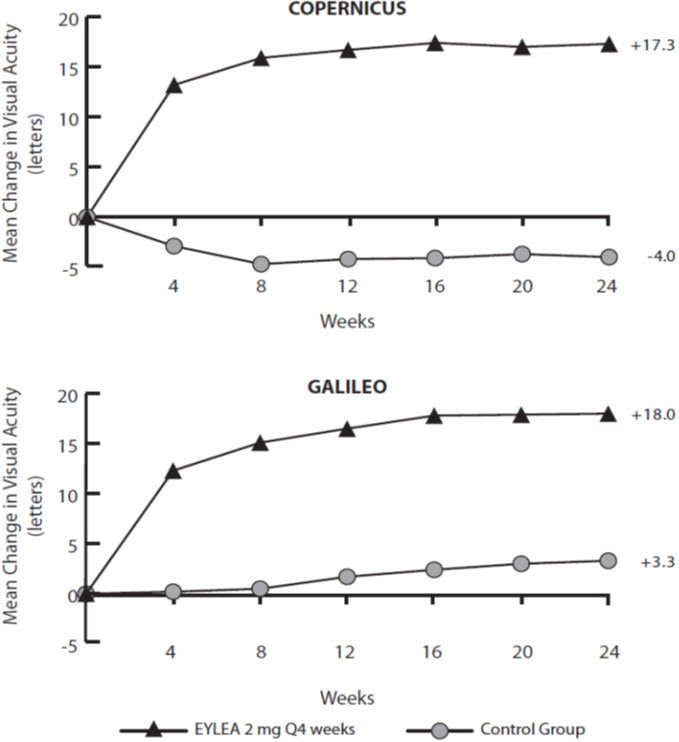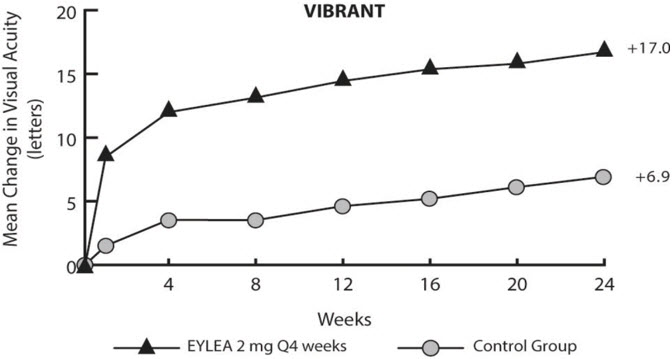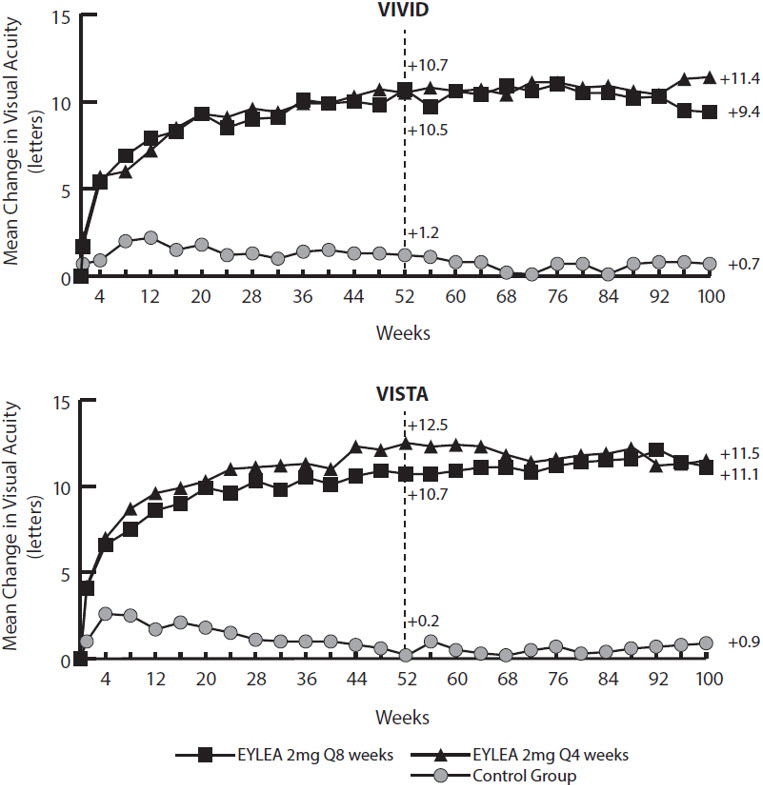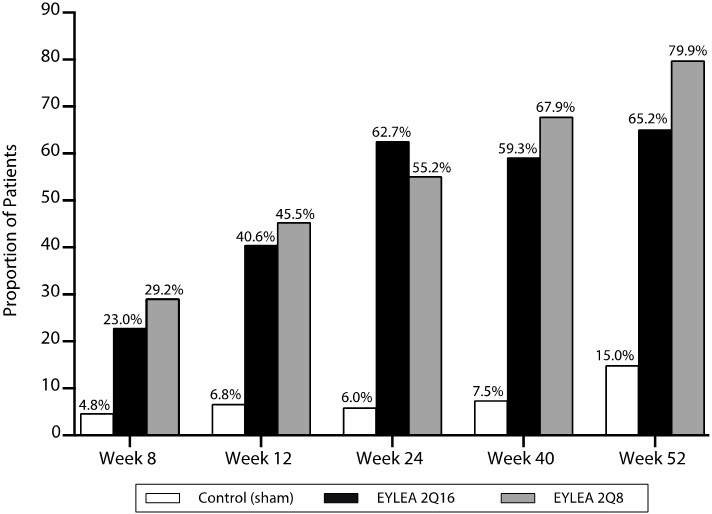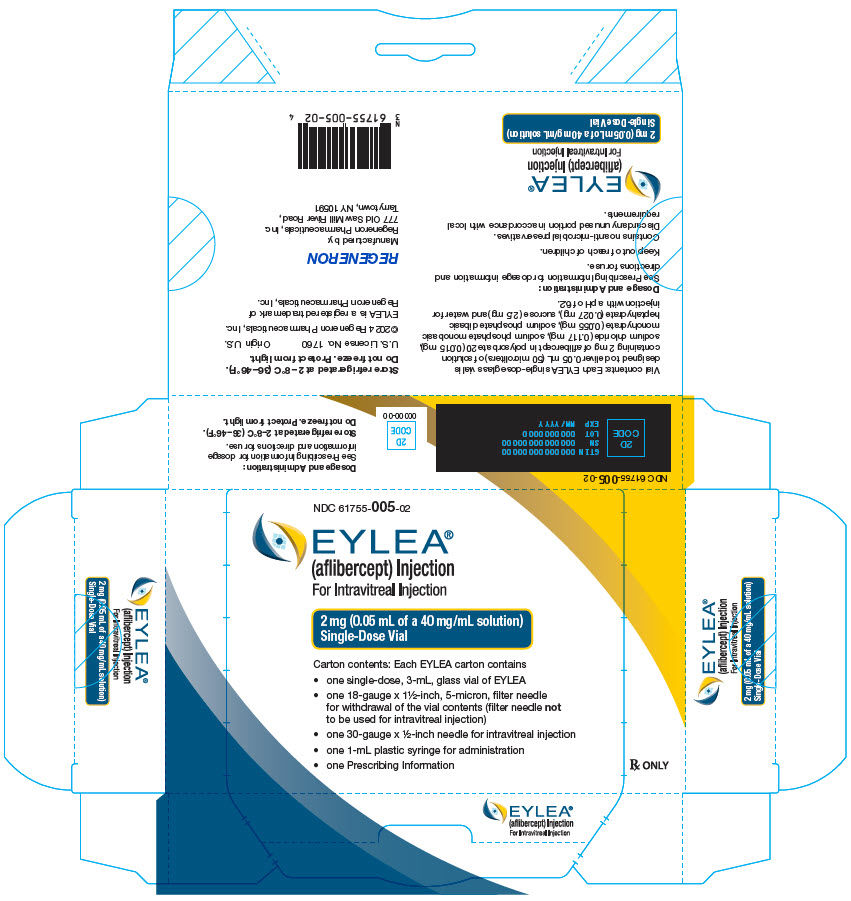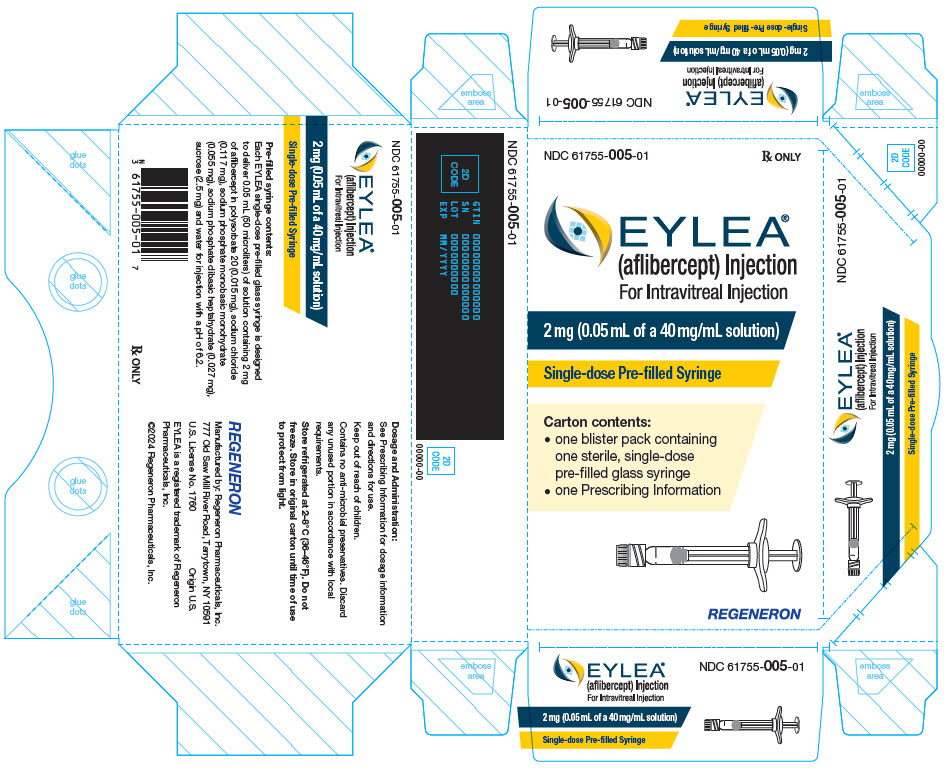 DRUG LABEL: EYLEA
NDC: 61755-005 | Form: INJECTION, SOLUTION
Manufacturer: Regeneron Pharmaceuticals, Inc.
Category: prescription | Type: HUMAN PRESCRIPTION DRUG LABEL
Date: 20251218

ACTIVE INGREDIENTS: aflibercept 40 mg/1 mL
INACTIVE INGREDIENTS: sodium phosphate; sodium chloride; polysorbate 20; sucrose

HIGHLIGHTS OF PRESCRIBING INFORMATION

These highlights do not include all the information needed to use EYLEA safely and effectively. See full prescribing information for EYLEA.
EYLEA® (aflibercept) injection, for intravitreal use
Initial U.S. Approval: 2011

RECENT MAJOR CHANGES

Warnings and Precautions (5.1) | 12/2023

1 INDICATIONS AND USAGE

EYLEA is a vascular endothelial growth factor (VEGF) inhibitor indicated for the treatment of patients with:

- Neovascular (Wet) Age-Related Macular Degeneration (AMD) (1.1)
- Macular Edema Following Retinal Vein Occlusion (RVO) (1.2)
- Diabetic Macular Edema (DME) (1.3)
- Diabetic Retinopathy (DR) (1.4)
- Retinopathy of Prematurity (ROP) (1.5)

2 DOSAGE AND ADMINISTRATION

- Neovascular (Wet) Age-Related Macular Degeneration (AMD)
  - The recommended dose for EYLEA is 2 mg (0.05 mL of 40 mg/mL solution) administered by intravitreal injection every 4 weeks (approximately every 28 days, monthly) for the first 3 months, followed by 2 mg (0.05 mL of 40 mg/mL solution) via intravitreal injection once every 8 weeks (2 months). (2.5)
  - Although EYLEA may be dosed as frequently as 2 mg every 4 weeks (approximately every 25 days, monthly), additional efficacy was not demonstrated in most patients when EYLEA was dosed every 4 weeks compared to every 8 weeks. Some patients may need every 4 week (monthly) dosing after the first 12 weeks (3 months). (2.5)
  - Although not as effective as the recommended every 8 week dosing regimen, patients may also be treated with one dose every 12 weeks after one year of effective therapy. Patients should be assessed regularly. (2.5)
- Macular Edema Following Retinal Vein Occlusion (RVO)
  - The recommended dose for EYLEA is 2 mg (0.05 mL of 40 mg/mL solution) administered by intravitreal injection once every 4 weeks (approximately every 25 days, monthly). (2.6)
- Diabetic Macular Edema (DME) and Diabetic Retinopathy (DR)
  - The recommended dose for EYLEA is 2 mg (0.05 mL of 40 mg/mL solution) administered by intravitreal injection every 4 weeks (approximately every 28 days, monthly) for the first 5 injections followed by 2 mg (0.05 mL of 40 mg/mL solution) via intravitreal injection once every 8 weeks (2 months). (2.7, 2.8)
  - Although EYLEA may be dosed as frequently as 2 mg every 4 weeks (approximately every 25 days, monthly), additional efficacy was not demonstrated in most patients when EYLEA was dosed every 4 weeks compared to every 8 weeks. Some patients may need every 4 week (monthly) dosing after the first 20 weeks (5 months). (2.7, 2.8)
- Retinopathy of Prematurity (ROP)
  - The recommended dose for EYLEA is 0.4 mg (0.01 mL or 10 microliters of 40 mg/mL solution) administered by intravitreal injection. Treatment may be given bilaterally on the same day. Injections may be repeated in each eye. The treatment interval between doses injected into the same eye should be at least 10 days. (2.9)

3 DOSAGE FORMS AND STRENGTHS

- Injection: 2 mg (0.05 mL of 40 mg/mL) solution in a single-dose pre-filled syringe (3)
- Injection: 2 mg (0.05 mL of 40 mg/mL) solution in a single-dose vial (3)

4 CONTRAINDICATIONS

- Ocular or periocular infection (4.1)
- Active intraocular inflammation (4.2)
- Hypersensitivity (4.3)

5 WARNINGS AND PRECAUTIONS

- Endophthalmitis, retinal detachments, and retinal vasculitis with or without occlusion may occur following intravitreal injections. Patients and/or caregivers should be instructed to report any signs and/or symptoms suggestive of endophthalmitis, retinal detachment, or retinal vasculitis without delay and should be managed appropriately. (5.1)
- Increases in intraocular pressure have been seen within 60 minutes of an intravitreal injection. (5.2)
- In infants with ROP, treatment with EYLEA will necessitate extended periods of ROP monitoring (5.3)
- There is a potential risk of arterial thromboembolic events following intravitreal use of VEGF inhibitors. (5.4)

6 ADVERSE REACTIONS

The most common adverse reactions (≥5%) reported in patients receiving EYLEA were conjunctival hemorrhage, eye pain, cataract, vitreous detachment, vitreous floaters, and intraocular pressure increased. (6.1)

To report SUSPECTED ADVERSE REACTIONS, contact Regeneron at 1-855-395-3248 or FDA at 1-800-FDA-1088 or www.fda.gov/medwatch.

FULL PRESCRIBING INFORMATION

1 INDICATIONS AND USAGE

EYLEA is indicated for the treatment of:

2 DOSAGE AND ADMINISTRATION

2.1 Important Injection Instructions

For ophthalmic intravitreal injection. EYLEA must only be administered by a qualified physician.

Pre-filled Syringe: A 30-gauge × ½-inch sterile injection needle is needed but not provided.

Vial: A 5-micron sterile filter needle (18-gauge × 1½-inch), a 1-mL Luer lock syringe and a 30-gauge × ½-inch sterile injection needle are needed.

EYLEA is available packaged as follows:

- Pre-filled Syringe
- Vial Kit with Injection Components (filter needle, syringe, injection needle)

[see How Supplied/Storage and Handling (16)].

2.2 Preparation for Administration – Pre-filled Syringe

The EYLEA pre-filled glass syringe is sterile and for one-time use in one eye only. Do not use the EYLEA pre-filled syringe for the treatment of ROP.

The pre-filled syringe should be inspected visually prior to administration. Do not use if particulates, cloudiness, or discoloration are visible, or if the package is open or damaged. The appearance of the syringe cap on the pre-filled syringe may vary (for example, color and design). Do not use if any part of the pre-filled syringe is damaged or if the syringe cap is detached from the Luer lock.

The intravitreal injection should be performed with a 30-gauge × ½-inch injection needle (not provided).

The pre-filled syringe contains more than the recommended dose of 2 mg aflibercept (equivalent to 50 microliters). The excess volume must be discarded prior to the administration.

PRE-FILLED SYRINGE DESCRIPTION – Figure 1:

Use aseptic technique to carry out the following steps:

1. PREPARE

When ready to administer EYLEA, open the carton and remove sterilized blister pack. Carefully peel open the sterilized blister pack ensuring the sterility of its contents. Keep the syringe in the sterile tray until you are ready for assembly.

2. REMOVE SYRINGE

Using aseptic technique, remove the syringe from the sterilized blister pack.

3. TWIST OFF SYRINGE CAP

Twist off (do not snap off) the syringe cap by holding the syringe in one hand and the syringe cap with the thumb and forefinger of the other hand (see Figure 2).

Note: To avoid compromising the sterility of the product, do not pull back on the plunger.

Figure 2:

4. ATTACH NEEDLE

Using aseptic technique, firmly twist a 30-gauge × ½-inch injection needle onto the Luer lock syringe tip (see Figure 3).

Figure 3:

Note: When ready to administer EYLEA, remove the plastic needle shield from the needle.

5. DISLODGE AIR BUBBLES

Holding the syringe with the needle pointing up, check the syringe for bubbles. If there are bubbles, gently tap the syringe with your finger until the bubbles rise to the top (see Figure 4).

Figure 4:

6. EXPEL AIR AND SET THE DOSE

To eliminate all bubbles and to expel excess drug, slowly depress the plunger rod to align the plunger dome edge (see Figure 5a) with the black dosing line on the syringe (equivalent to 50 microliters) (see Figure 5b).

Figure 5a:

Figure 5b:

7. The pre-filled syringe is for one-time use in one eye only. After injection any unused product must be discarded.

2.3 Preparation for Administration - Vial

EYLEA should be inspected visually prior to administration. If particulates, cloudiness, or discoloration are visible, the vial must not be used.

The glass vial is for one-time use in one eye only.

Use aseptic technique to carry out the following preparation steps:

Prepare for intravitreal injection with the following medical devices for single use:

- a 5-micron sterile filter needle (18-gauge × 1½-inch)
- a 1-mL sterile Luer lock syringe with marking to measure 0.05 mL for adults or 0.01 mL for pre-term infants with ROP
- a sterile injection needle (30-gauge × ½-inch)

1. Remove the protective plastic cap from the vial (see Figure 6).
  Figure 6:
2. Clean the top of the vial with an alcohol wipe (see Figure 7).
  Figure 7:
3. Remove the 18-gauge × 1½-inch, 5-micron, filter needle and the 1-mL syringe from their packaging. Attach the filter needle to the syringe by twisting it onto the Luer lock syringe tip (see Figure 8).
  Figure 8:
4. Push the filter needle into the center of the vial stopper until the needle is completely inserted into the vial and the tip touches the bottom or bottom edge of the vial.
5. Using aseptic technique withdraw all of the EYLEA vial contents into the syringe, keeping the vial in an upright position, slightly inclined to ease complete withdrawal. To deter the introduction of air, ensure the bevel of the filter needle is submerged into the liquid. Continue to tilt the vial during withdrawal keeping the bevel of the filter needle submerged in the liquid (see Figure 9a and Figure 9b).
  Figure 9a:
  Figure 9b:
6. Ensure that the plunger rod is drawn sufficiently back when emptying the vial in order to completely empty the filter needle.
7. Remove the filter needle from the syringe and properly dispose of the filter needle. Note: Filter needle is not to be used for intravitreal injection.
8. Remove the 30-gauge × ½-inch injection needle from its packaging and attach the injection needle to the syringe by firmly twisting the injection needle onto the Luer lock syringe tip (see Figure 10).
  Figure 10:
9. When ready to administer EYLEA, remove the plastic needle shield from the needle.
10. Holding the syringe with the needle pointing up, check the syringe for bubbles. If there are bubbles, gently tap the syringe with your finger until the bubbles rise to the top (see Figure 11).
  Figure 11:
  Administration in Adults:
11. To eliminate all of the bubbles and to expel excess drug, SLOWLY depress the plunger rod so that the plunger edge aligns with the line that marks 0.05 mL on the syringe (see Figure 12a and Figure 12b).

2.4 Injection Procedure for Adults

The intravitreal injection procedure should be carried out under controlled aseptic conditions, which include surgical hand disinfection and the use of sterile gloves, a sterile drape, and a sterile eyelid speculum (or equivalent). Adequate anesthesia and a topical broad–spectrum microbicide should be given prior to the injection.

Pre-filled syringe: Inject by pressing the plunger carefully and with constant pressure. Do not apply additional pressure once the plunger has reached the bottom of the syringe. A small residual volume may remain in the syringe after a full dose has been injected. This is normal. Do not administer any residual solution observed in the syringe.

Immediately following the intravitreal injection, patients should be monitored for elevation in intraocular pressure. Appropriate monitoring may consist of a check for perfusion of the optic nerve head or tonometry. If required, a sterile paracentesis needle should be available.

Following intravitreal injection, patients and/or caregivers should be instructed to report any signs and/or symptoms suggestive of endophthalmitis or retinal detachment (e.g., eye pain, redness of the eye, photophobia, blurring of vision) without delay [see Patient Counseling Information (17)].

Each sterile, pre-filled syringe or vial should only be used for the treatment of a single eye. If the contralateral eye requires treatment, a new sterile, pre-filled syringe or vial should be used and the sterile field, syringe, gloves, drapes, eyelid speculum, filter, and injection needles should be changed before EYLEA is administered to the other eye.

After injection, any unused product must be discarded.

2.5 Neovascular (Wet) Age-Related Macular Degeneration (AMD)

The recommended dose for EYLEA is 2 mg (0.05 mL of 40 mg/mL solution) administered by intravitreal injection every 4 weeks (approximately every 28 days, monthly) for the first 12 weeks (3 months), followed by 2 mg (0.05 mL of 40 mg/mL solution) via intravitreal injection once every 8 weeks (2 months). Although EYLEA may be dosed as frequently as 2 mg every 4 weeks (approximately every 25 days, monthly), additional efficacy was not demonstrated in most patients when EYLEA was dosed every 4 weeks compared to every 8 weeks [see Clinical Studies (14.1)]. Some patients may need every 4 week (monthly) dosing after the first 12 weeks (3 months). Although not as effective as the recommended every 8 week dosing regimen, patients may also be treated with one dose every 12 weeks after one year of effective therapy. Patients should be assessed regularly.

2.6 Macular Edema Following Retinal Vein Occlusion (RVO)

The recommended dose for EYLEA is 2 mg (0.05 mL of 40 mg/mL solution) administered by intravitreal injection once every 4 weeks (approximately every 25 days, monthly) [see Clinical Studies (14.2), (14.3)].

2.7 Diabetic Macular Edema (DME)

The recommended dose for EYLEA is 2 mg (0.05 mL of 40 mg/mL solution) administered by intravitreal injection every 4 weeks (approximately every 28 days, monthly) for the first 5 injections, followed by 2 mg (0.05 mL of 40 mg/mL solution) via intravitreal injection once every 8 weeks (2 months). Although EYLEA may be dosed as frequently as 2 mg every 4 weeks (approximately every 25 days, monthly), additional efficacy was not demonstrated in most patients when EYLEA was dosed every 4 weeks compared to every 8 weeks [see Clinical Studies (14.4)]. Some patients may need every 4 week (monthly) dosing after the first 20 weeks (5 months).

2.8 Diabetic Retinopathy (DR)

The recommended dose for EYLEA is 2 mg (0.05 mL of 40 mg/mL solution) administered by intravitreal injection every 4 weeks (approximately every 28 days, monthly) for the first 5 injections, followed by 2 mg (0.05 mL of 40 mg/mL solution) via intravitreal injection once every 8 weeks (2 months). Although EYLEA may be dosed as frequently as 2 mg every 4 weeks (approximately every 25 days, monthly), additional efficacy was not demonstrated in most patients when EYLEA was dosed every 4 weeks compared to every 8 weeks [see Clinical Studies (14.5)]. Some patients may need every 4 week (monthly) dosing after the first 20 weeks (5 months).

2.9 Retinopathy of Prematurity (ROP)

Recommended Dosage

The recommended dose for EYLEA is 0.4 mg (0.01 mL or 10 microliters of 40 mg/mL solution) administered by intravitreal injection. Treatment is initiated with a single injection per eligible eye and may be given bilaterally on the same day. Injections may be repeated in each eye. The treatment interval between doses injected into the same eye should be at least 10 days [see Clinical Pharmacology (12.3) and Clinical Studies (14.6)].

Administration Instructions in Pre-Term Infants with ROP

The intravitreal injection procedure should be carried out under controlled aseptic conditions, which include surgical hand disinfection and the use of sterile gloves, a sterile drape, and a sterile eyelid speculum (or equivalent). Adequate anesthesia and a topical broad–spectrum microbicide should be given prior to the injection.

Immediately following the intravitreal injection, patients should be monitored for elevation in intraocular pressure. Appropriate monitoring may consist of a check for perfusion of the optic nerve head or tonometry. If required, a sterile paracentesis needle should be available.

Following intravitreal injection, patients and/or caregivers should be instructed to report any signs and/or symptoms suggestive of endophthalmitis or retinal detachment (e.g., eye pain, redness of the eye, photophobia, blurring of vision) without delay [see Patient Counseling Information (17)].

Each sterile vial should only be used for the treatment of a single eye. Do not use the EYLEA pre-filled syringe for the treatment of ROP. If the contralateral eye requires treatment, a new sterile vial should be used and the sterile field, syringe, gloves, drapes, eyelid speculum, filter, and injection needles should be changed before EYLEA is administered to the other eye.

Follow steps 1-10 listed in 2.3 Preparation for Administration – Vial.

11 . To eliminate all of the bubbles and to expel excess drug, SLOWLY depress the plunger rod so that the plunger edge aligns with the line that marks 0.01 mL on the syringe (see Figure 13a and Figure 13b).

For the treatment of ROP, the injection needle should be inserted into the eye 1 mm from the limbus with the needle angled to avoid the lens and to avoid the retina.

After injection, any unused product must be discarded.

3 DOSAGE FORMS AND STRENGTHS

EYLEA is a clear, colorless to pale yellow solution available as:

- Injection: 2 mg (0.05 mL of a 40 mg/mL solution) in a single-dose pre-filled glass syringe
- Injection: 2 mg (0.05 mL of a 40 mg/mL solution) in a single-dose glass vial

4 CONTRAINDICATIONS

4.1 Ocular or Periocular Infections

EYLEA is contraindicated in patients with ocular or periocular infections.

4.2 Active Intraocular Inflammation

EYLEA is contraindicated in patients with active intraocular inflammation.

4.3 Hypersensitivity

EYLEA is contraindicated in patients with known hypersensitivity to aflibercept or any of the excipients in EYLEA. Hypersensitivity reactions may manifest as rash, pruritus, urticaria, severe anaphylactic/anaphylactoid reactions, or severe intraocular inflammation.

5 WARNINGS AND PRECAUTIONS

5.1 Endophthalmitis, Retinal Detachments, and Retinal Vasculitis with or without Occlusion

Intravitreal injections, including those with EYLEA, have been associated with endophthalmitis and retinal detachments [see Adverse Reactions (6.1)] and, more rarely, retinal vasculitis with or without occlusion [see Adverse Reactions (6.2)]. Proper aseptic injection technique must always be used when administering EYLEA. Patients and/or caregivers should be instructed to report any signs and/or symptoms suggestive of endophthalmitis, retinal detachment, or retinal vasculitis without delay and should be managed appropriately [see Dosage and Administration (2.4) and Patient Counseling Information (17)].

5.2 Increase in Intraocular Pressure

Acute increases in intraocular pressure have been seen within 60 minutes of intravitreal injection, including with EYLEA [see Adverse Reactions (6.1)]. Sustained increases in intraocular pressure have also been reported after repeated intravitreal dosing with vascular endothelial growth factor (VEGF) inhibitors. Intraocular pressure and the perfusion of the optic nerve head should be monitored and managed appropriately [see Dosage and Administration (2.4)].

5.3 Extended Monitoring and Additional Treatment in ROP

Reactivation of abnormal angiogenesis and tortuosity may occur following treatment with EYLEA. Infants should be monitored closely after injection with EYLEA until retinal vascularization has completed or until the examiner is assured that reactivation of ROP will not occur. In infants with ROP, treatment with EYLEA will necessitate extended periods of ROP monitoring and additional EYLEA injections and/or laser treatments may be necessary.

5.4 Thromboembolic Events

There is a potential risk of arterial thromboembolic events (ATEs) following intravitreal use of VEGF inhibitors, including EYLEA. ATEs are defined as nonfatal stroke, nonfatal myocardial infarction, or vascular death (including deaths of unknown cause). The incidence of reported thromboembolic events in wet AMD studies during the first year was 1.8% (32 out of 1824) in the combined group of patients treated with EYLEA compared with 1.5% (9 out of 595) in patients treated with ranibizumab; through 96 weeks, the incidence was 3.3% (60 out of 1824) in the EYLEA group compared with 3.2% (19 out of 595) in the ranibizumab group. The incidence in the DME studies from baseline to week 52 was 3.3% (19 out of 578) in the combined group of patients treated with EYLEA compared with 2.8% (8 out of 287) in the control group; from baseline to week 100, the incidence was 6.4% (37 out of 578) in the combined group of patients treated with EYLEA compared with 4.2% (12 out of 287) in the control group. There were no reported thromboembolic events in the patients treated with EYLEA in the first six months of the RVO studies.

6 ADVERSE REACTIONS

The following potentially serious adverse reactions are described elsewhere in the labeling:

- Hypersensitivity [see Contraindications (4.3)]
- Endophthalmitis, Retinal Detachments, and Retinal Vasculitis with or without Occlusion [see Warnings and Precautions (5.1)]
- Increase in intraocular pressure [see Warnings and Precautions (5.2)]
- Thromboembolic events [see Warnings and Precautions (5.4)]

6.1 Clinical Trials Experience

Because clinical trials are conducted under widely varying conditions, adverse reaction rates observed in the clinical trials of a drug cannot be directly compared to rates in other clinical trials of the same or another drug and may not reflect the rates observed in practice.

A total of 2980 adult patients treated with EYLEA constituted the safety population in eight phase 3 studies. Among those, 2379 patients were treated with the recommended dose of 2 mg. Serious adverse reactions related to the injection procedure have occurred in <0.1% of intravitreal injections with EYLEA including endophthalmitis and retinal detachment. The most common adverse reactions (≥5%) reported in patients receiving EYLEA were conjunctival hemorrhage, eye pain, cataract, vitreous detachment, vitreous floaters, and intraocular pressure increased.

Neovascular (Wet) Age-Related Macular Degeneration (AMD)

The data described below reflect exposure to EYLEA in 1824 patients with wet AMD, including 1223 patients treated with the 2-mg dose, in 2 double-masked, controlled clinical studies (VIEW1 and VIEW2) for 24 months (with active control in year 1) [see Clinical Studies (14.1)].

Safety data observed in the EYLEA group in a 52-week, double-masked, Phase 2 study were consistent with these results.

Table 1: Most Common Adverse Reactions (≥1%) in Wet AMD Studies
Adverse Reactions | Baseline to Week 52 |  | Baseline to Week 96
Adverse Reactions | EYLEA (N=1824) | Active Control (ranibizumab) (N=595) | EYLEA (N=1824) | Control (ranibizumab) (N=595)
Conjunctival hemorrhage | 25% | 28% | 27% | 30%
Eye pain | 9% | 9% | 10% | 10%
Cataract | 7% | 7% | 13% | 10%
Vitreous detachment | 6% | 6% | 8% | 8%
Vitreous floaters | 6% | 7% | 8% | 10%
Intraocular pressure increased | 5% | 7% | 7% | 11%
Ocular hyperemia | 4% | 8% | 5% | 10%
Corneal epithelium defect | 4% | 5% | 5% | 6%
Detachment of the retinal pigment epithelium | 3% | 3% | 5% | 5%
Injection site pain | 3% | 3% | 3% | 4%
Foreign body sensation in eyes | 3% | 4% | 4% | 4%
Lacrimation increased | 3% | 1% | 4% | 2%
Vision blurred | 2% | 2% | 4% | 3%
Intraocular inflammation | 2% | 3% | 3% | 4%
Retinal pigment epithelium tear | 2% | 1% | 2% | 2%
Injection site hemorrhage | 1% | 2% | 2% | 2%
Eyelid edema | 1% | 2% | 2% | 3%
Corneal edema | 1% | 1% | 1% | 1%
Retinal detachment | <1% | <1% | 1% | 1%

Less common serious adverse reactions reported in <1% of the patients treated with EYLEA were hypersensitivity, retinal tear, and endophthalmitis.

Macular Edema Following Retinal Vein Occlusion (RVO)

The data described below reflect 6 months exposure to EYLEA with a monthly 2 mg dose in 218 patients following central retinal vein occlusion (CRVO) in 2 clinical studies (COPERNICUS and GALILEO) and 91 patients following branch retinal vein occlusion (BRVO) in one clinical study (VIBRANT) [see Clinical Studies (14.2), (14.3)].

Table 2: Most Common Adverse Reactions (≥1%) in RVO Studies
Adverse Reactions | CRVO |  | BRVO
 | EYLEA (N=218) | Control (N=142) | EYLEA (N=91) | Control (N=92)
Eye pain | 13% | 5% | 4% | 5%
Conjunctival hemorrhage | 12% | 11% | 20% | 4%
Intraocular pressure increased | 8% | 6% | 2% | 0%
Corneal epithelium defect | 5% | 4% | 2% | 0%
Vitreous floaters | 5% | 1% | 1% | 0%
Ocular hyperemia | 5% | 3% | 2% | 2%
Foreign body sensation in eyes | 3% | 5% | 3% | 0%
Vitreous detachment | 3% | 4% | 2% | 0%
Lacrimation increased | 3% | 4% | 3% | 0%
Injection site pain | 3% | 1% | 1% | 0%
Vision blurred | 1% | <1% | 1% | 1%
Intraocular inflammation | 1% | 1% | 0% | 0%
Cataract | <1% | 1% | 5% | 0%
Eyelid edema | <1% | 1% | 1% | 0%

Less common adverse reactions reported in <1% of the patients treated with EYLEA in the CRVO studies were corneal edema, retinal tear, hypersensitivity, and endophthalmitis.

Diabetic Macular Edema (DME) and Diabetic Retinopathy (DR)

The data described below reflect exposure to EYLEA in 578 patients with DME treated with the 2-mg dose in 2 double-masked, controlled clinical studies (VIVID and VISTA) from baseline to week 52 and from baseline to week 100 [see Clinical Studies (14.4)].

Table 3: Most Common Adverse Reactions (≥1%) in DME Studies
Adverse Reactions | Baseline to Week 52 |  | Baseline to Week 100
 | EYLEA (N=578) | Control (N=287) | EYLEA (N=578) | Control (N=287)
Conjunctival hemorrhage | 28% | 17% | 31% | 21%
Eye pain | 9% | 6% | 11% | 9%
Cataract | 8% | 9% | 19% | 17%
Vitreous floaters | 6% | 3% | 8% | 6%
Corneal epithelium defect | 5% | 3% | 7% | 5%
Intraocular pressure increased | 5% | 3% | 9% | 5%
Ocular hyperemia | 5% | 6% | 5% | 6%
Vitreous detachment | 3% | 3% | 8% | 6%
Foreign body sensation in eyes | 3% | 3% | 3% | 3%
Lacrimation increased | 3% | 2% | 4% | 2%
Vision blurred | 2% | 2% | 3% | 4%
Intraocular inflammation | 2% | <1% | 3% | 1%
Injection site pain | 2% | <1% | 2% | <1%
Eyelid edema | <1% | 1% | 2% | 1%

Less common adverse reactions reported in <1% of the patients treated with EYLEA were hypersensitivity, retinal detachment, retinal tear, corneal edema, and injection site hemorrhage.

Safety data observed in 269 patients with nonproliferative diabetic retinopathy (NPDR) through week 52 in the PANORAMA trial were consistent with those seen in the phase 3 VIVID and VISTA trials (see Table 3 above).

Retinopathy of Prematurity (ROP)

The data described below reflect exposure to EYLEA in 168 pre-term infants with ROP randomized to EYLEA and treated with the 0.4 mg dose in 2 clinical studies (BUTTERFLEYE and FIREFLEYE/FIREFLEYE NEXT) from time of first administration up to 52 weeks of chronological age [see Clinical Studies (14.6)]. Adverse reactions established for adult indications are considered applicable to pre-term infants with ROP, though not all were observed in the clinical studies.

Table 4: Adverse Reactions in ROP Studies [Five year follow-up studies are ongoing through 2026]
Adverse Reactions | Baseline to 52 weeks of chronological age |  | Baseline to 52 weeks of chronological age
Adverse Reactions | BUTTERFLEYE |  | FIREFLEYE/FIREFLEYE NEXT
 | EYLEA (N=93) | Laser (N=27) | EYLEA (N=75) | Laser (N=38)
Retinal detachment | 6% | 7% | 5% | 5%
Conjunctival hemorrhage [Includes injection site hemorrhage] | 5% | 0% | 9% | 0%
Intraocular pressure increased | 0% | 0% | 4% | 0%
Corneal epithelium defect | 1% | 0% | 0% | 0%
Eyelid edema | 0% | 4% | 3% | 8%
Corneal edema | 0% | 0% | 1% | 3%
Lenticular Opacities | 0% | 0% | 1% | 0%

6.2 Postmarketing Experience

The following adverse reactions have been identified during postapproval use of aflibercept. Because these reactions are reported voluntarily from a population of uncertain size, it is not always possible to reliably estimate their frequency or establish a causal relationship to drug exposure.

Eye disorders:

- Retinal vasculitis and occlusive retinal vasculitis related to intravitreal injection with aflibercept (reported at a rate of 0.6 and 0.2 per 1 million injections, respectively, based on postmarketing experience from November 2011 until November 2023).
- Scleritis.

8 USE IN SPECIFIC POPULATIONS

8.1 Pregnancy

Risk Summary

Adequate and well-controlled studies with EYLEA have not been conducted in pregnant women. Aflibercept produced adverse embryofetal effects in rabbits, including external, visceral, and skeletal malformations. A fetal No Observed Adverse Effect Level (NOAEL) was not identified. At the lowest dose shown to produce adverse embryofetal effects, systemic exposures (based on AUC for free aflibercept) were approximately 6 times higher than AUC values observed in humans after a single intravitreal treatment at the recommended clinical dose [see Animal Data].

Animal reproduction studies are not always predictive of human response, and it is not known whether EYLEA can cause fetal harm when administered to a pregnant woman. Based on the anti-VEGF mechanism of action for aflibercept [see Clinical Pharmacology (12.1)], treatment with EYLEA may pose a risk to human embryofetal development. EYLEA should be used during pregnancy only if the potential benefit justifies the potential risk to the fetus.

All pregnancies have a background risk of birth defect, loss, or other adverse outcomes. The background risk of major birth defects and miscarriage for the indicated population is unknown. In the U.S. general population, the estimated background risk of major birth defects and miscarriage in clinically recognized pregnancies is 2-4% and 15-20%, respectively.

Data

Animal Data

In two embryofetal development studies, aflibercept produced adverse embryofetal effects when administered every three days during organogenesis to pregnant rabbits at intravenous doses ≥3 mg per kg, or every six days during organogenesis at subcutaneous doses ≥0.1 mg per kg.

Adverse embryofetal effects included increased incidences of postimplantation loss and fetal malformations, including anasarca, umbilical hernia, diaphragmatic hernia, gastroschisis, cleft palate, ectrodactyly, intestinal atresia, spina bifida, encephalomeningocele, heart and major vessel defects, and skeletal malformations (fused vertebrae, sternebrae, and ribs; supernumerary vertebral arches and ribs; and incomplete ossification). The maternal No Observed Adverse Effect Level (NOAEL) in these studies was 3 mg per kg. Aflibercept produced fetal malformations at all doses assessed in rabbits and the fetal NOAEL was not identified. At the lowest dose shown to produce adverse embryofetal effects in rabbits (0.1 mg per kg), systemic exposure (AUC) of free aflibercept was approximately 6 times higher than systemic exposure (AUC) observed in adult patients after a single intravitreal dose of 2 mg.

8.2 Lactation

Risk Summary

There is no information regarding the presence of aflibercept in human milk, the effects of the drug on the breastfed infant, or the effects of the drug on milk production/excretion. Because many drugs are excreted in human milk, and because the potential for absorption and harm to infant growth and development exists, EYLEA is not recommended during breastfeeding.

The developmental and health benefits of breastfeeding should be considered along with the mother's clinical need for EYLEA and any potential adverse effects on the breastfed child from EYLEA.

8.3 Females and Males of Reproductive Potential

Contraception

Females of reproductive potential are advised to use effective contraception prior to the initial dose, during treatment, and for at least 3 months after the last intravitreal injection of EYLEA.

Infertility

There are no data regarding the effects of EYLEA on human fertility. Aflibercept adversely affected female and male reproductive systems in cynomolgus monkeys when administered by intravenous injection at a dose approximately 1500 times higher than the systemic level observed in adult patients with an intravitreal dose of 2 mg. A No Observed Adverse Effect Level (NOAEL) was not identified. These findings were reversible within 20 weeks after cessation of treatment [see Nonclinical Toxicology (13.1)].

8.4 Pediatric Use

The safety and effectiveness of EYLEA have been demonstrated in two clinical studies of pre-term infants with ROP.

These two studies randomized pre-term infants between initial treatment with EYLEA or laser. Efficacy of each treatment is supported by the demonstration of a clinical course which was better than would have been expected without treatment [see Dosage and Administration (2.9), Adverse Reactions (6.1), Clinical Pharmacology (12.3) and Clinical Studies (14.6)].

8.5 Geriatric Use

In the clinical studies, approximately 76% (2049/2701) of patients randomized to treatment with EYLEA were ≥65 years of age and approximately 46% (1250/2701) were ≥75 years of age. No significant differences in efficacy or safety were seen with increasing age in these studies.

10 OVERDOSAGE

Overdosing with increased injection volume may increase intraocular pressure. Therefore, in case of overdosage, intraocular pressure should be monitored and if deemed necessary by the treating physician, adequate treatment should be initiated.

11 DESCRIPTION

Aflibercept is a recombinant fusion protein consisting of portions of human VEGF receptors 1 and 2 extracellular domains fused to the Fc portion of human IgG1 formulated as an iso-osmotic solution for intravitreal administration. Aflibercept is a dimeric glycoprotein with a protein molecular weight of 97 kilodaltons (kDa) and contains glycosylation, constituting an additional 15% of the total molecular mass, resulting in a total molecular weight of 115 kDa. Aflibercept is produced in recombinant Chinese hamster ovary (CHO) cells.

EYLEA (aflibercept) Injection is a sterile, clear, and colorless to pale yellow solution. EYLEA does not contain anti-microbial preservative and is supplied as a sterile, aqueous solution for intravitreal injection in a single-dose pre-filled glass syringe or a single-dose glass vial designed to deliver 0.05 mL (50 microliters) of solution containing 2 mg of aflibercept in polysorbate 20 (0.015 mg), sodium chloride (0.117 mg), sodium phosphate monobasic monohydrate (0.055 mg), sodium phosphate dibasic heptahydrate (0.027 mg), sucrose (2.5 mg) and water for injection with a pH of 6.2.

12 CLINICAL PHARMACOLOGY

12.1 Mechanism of Action

Vascular endothelial growth factor-A (VEGF-A) and placental growth factor (PlGF) are members of the VEGF family of angiogenic factors that can act as mitogenic, chemotactic, and vascular permeability factors for endothelial cells. VEGF acts via two receptor tyrosine kinases, VEGFR-1 and VEGFR-2, present on the surface of endothelial cells. PlGF binds only to VEGFR-1, which is also present on the surface of leucocytes. Activation of these receptors by VEGF-A can result in neovascularization and vascular permeability.

Aflibercept acts as a soluble decoy receptor that binds VEGF-A and PlGF, and thereby can inhibit the binding and activation of these cognate VEGF receptors.

12.2 Pharmacodynamics

Neovascular (Wet) Age-Related Macular Degeneration (AMD)

In the clinical studies anatomic measures of disease activity improved similarly in all treatment groups from baseline to week 52. Anatomic data were not used to influence treatment decisions during the first year.

Macular Edema Following Retinal Vein Occlusion (RVO)

Reductions in mean retinal thickness were observed in COPERNICUS, GALILEO, and VIBRANT at week 24 compared to baseline. Anatomic data were not used to influence treatment decisions [see Clinical Studies (14.2), (14.3)].

Diabetic Macular Edema (DME)

Reductions in mean retinal thickness were observed in VIVID and VISTA at weeks 52 and 100 compared to baseline. Anatomic data were not used to influence EYLEA treatment decisions [see Clinical Studies (14.4)].

12.3 Pharmacokinetics

EYLEA is administered intravitreally to exert local effects in the eye. In patients with wet AMD, RVO, or DME, following intravitreal administration of EYLEA, a fraction of the administered dose is expected to bind with endogenous VEGF in the eye to form an inactive aflibercept: VEGF complex. Once absorbed into the systemic circulation, aflibercept presents in the plasma as free aflibercept (unbound to VEGF) and a more predominant stable inactive form with circulating endogenous VEGF (i.e., aflibercept: VEGF complex).

Absorption/Distribution

Following intravitreal administration of 2 mg per eye of EYLEA to patients with wet AMD, RVO, and DME, the mean Cmax of free aflibercept in the plasma was 0.02 mcg/mL (range: 0 to 0.054 mcg/mL), 0.05 mcg/mL (range: 0 to 0.081 mcg/mL), and 0.03 mcg/mL (range: 0 to 0.076 mcg/mL), respectively and was attained in 1 to 3 days. The free aflibercept plasma concentrations were undetectable two weeks post-dosing in all patients. Aflibercept did not accumulate in plasma when administered as repeated doses intravitreally every 4 weeks. It is estimated that after intravitreal administration of 2 mg to patients, the mean maximum plasma concentration of free aflibercept is more than 100 fold lower than the concentration of aflibercept required to half-maximally bind systemic VEGF.

The volume of distribution of free aflibercept following intravenous (I.V.) administration of aflibercept has been determined to be approximately 6L.

Metabolism/Elimination

Aflibercept is a therapeutic protein and no drug metabolism studies have been conducted. Aflibercept is expected to undergo elimination through both target-mediated disposition via binding to free endogenous VEGF and metabolism via proteolysis. The terminal elimination half-life (t1/2) of free aflibercept in plasma was approximately 5 to 6 days after I.V. administration of doses of 2 to 4 mg/kg aflibercept.

Specific Populations

Pediatric Patients

Pharmacokinetics of aflibercept were evaluated in pre-term infants with ROP at a dose of 0.4 mg aflibercept (per eye) administered unilaterally or bilaterally. In the BUTTERFLEYE study, mean concentrations of free aflibercept in plasma declined from a maximum of 0.583 mcg/mL at Day 1 to 0.0406 mcg/mL at Day 28 in bilaterally treated patients.

In the FIREFLEYE study, mean concentrations of free aflibercept in plasma for all patients (bilateral and unilateral administration combined) declined from a maximum of 0.481 mcg/mL at Day 1 to 0.13 mcg/mL at Day 28. Concentrations of free aflibercept in plasma subsequently declined to values below or close to the lower limit of quantitation within approximately 8 weeks.

Following an IVT dose of aflibercept 0.4 mg per eye given bilaterally at 10 or 14 day intervals, the population pharmacokinetic estimated mean maximal accumulation ratio of free aflibercept in plasma was approximately 2.0 and 1.4. No accumulation of free aflibercept in plasma is expected for IVT doses of 0.4 mg per eye given bilaterally at dosing intervals of 21 days or longer.

Renal Impairment

Pharmacokinetic analysis of a subgroup of patients (n=492) in one wet AMD study, of which 43% had renal impairment (mild n=120, moderate n=74, and severe n=16), revealed no differences with respect to plasma concentrations of free aflibercept after intravitreal administration every 4 or 8 weeks. Similar results were seen in patients in a RVO study and in patients in a DME study. No dose adjustment based on renal impairment status is needed for either wet AMD, RVO, or DME patients.

Other

No dosage modification is required based on gender or in the elderly.

12.6 Immunogenicity

As with all therapeutic proteins, there is a potential for an immune response in patients treated with EYLEA. The immunogenicity of EYLEA was evaluated in serum samples. The immunogenicity data reflect the percentage of patients whose test results were considered positive for antibodies to EYLEA in immunoassays. The detection of an immune response is highly dependent on the sensitivity and specificity of the assays used, sample handling, timing of sample collection, concomitant medications, and underlying disease. For these reasons, comparison of the incidence of antibodies to EYLEA with the incidence of antibodies to other products may be misleading.

In the wet AMD, RVO, and DME studies, the pre-treatment incidence of immunoreactivity to EYLEA was approximately 1% to 3% across treatment groups. After dosing with EYLEA for 24-100 weeks, antibodies to EYLEA were detected in a similar percentage range of patients. Similarly, after unilateral or bilateral dosing in pediatric ROP studies, antibodies to EYLEA were detected in less than 1% of patients.

There were no differences in efficacy or safety between patients with or without immunoreactivity.

13 NONCLINICAL TOXICOLOGY

13.1 Carcinogenesis, Mutagenesis, Impairment of Fertility

No studies have been conducted on the mutagenic or carcinogenic potential of aflibercept. Effects on male and female fertility were assessed as part of a 6-month study in monkeys with intravenous administration of aflibercept at weekly doses ranging from 3 to 30 mg per kg. Absent or irregular menses associated with alterations in female reproductive hormone levels and changes in sperm morphology and motility were observed at all dose levels. In addition, females showed decreased ovarian and uterine weight accompanied by compromised luteal development and reduction of maturing follicles. These changes correlated with uterine and vaginal atrophy. A No Observed Adverse Effect Level (NOAEL) was not identified. Intravenous administration of the lowest dose of aflibercept assessed in monkeys (3 mg per kg) resulted in systemic exposure (AUC) for free aflibercept that was approximately 1500 times higher than the systemic exposure observed in adult patients after an intravitreal dose of 2 mg. All changes were reversible within 20 weeks after cessation of treatment.

13.2 Animal Toxicology and/or Pharmacology

Erosions and ulcerations of the respiratory epithelium in nasal turbinates in monkeys treated with aflibercept intravitreally were observed at intravitreal doses of 2 or 4 mg per eye. At the NOAEL of 0.5 mg per eye in monkeys, the systemic exposure (AUC) was 56 times higher than the exposure observed in adult patients after an intravitreal dose of 2 mg and 2-fold higher based on Cmax when compared to corresponding values observed in pre-term infants from FIREFLEYE. Similar effects were not seen in other clinical studies [see Clinical Studies (14)].

14 CLINICAL STUDIES

14.1 Neovascular (Wet) Age-Related Macular Degeneration (AMD)

The safety and efficacy of EYLEA were assessed in two randomized, multi-center, double-masked, active-controlled studies in patients with wet AMD. A total of 2412 patients were treated and evaluable for efficacy (1817 with EYLEA) in the two studies (VIEW1 and VIEW2). In each study, up to week 52, patients were randomly assigned in a 1:1:1:1 ratio to 1 of 4 dosing regimens: 1) EYLEA administered 2 mg every 8 weeks following 3 initial monthly doses (EYLEA 2Q8); 2) EYLEA administered 2 mg every 4 weeks (EYLEA 2Q4); 3) EYLEA 0.5 mg administered every 4 weeks (EYLEA 0.5Q4); and 4) ranibizumab administered 0.5 mg every 4 weeks (ranibizumab 0.5 mg Q4). Protocol-specified visits occurred every 28±3 days. Patient ages ranged from 49 to 99 years with a mean of 76 years.

In both studies, the primary efficacy endpoint was the proportion of patients who maintained vision, defined as losing fewer than 15 letters of visual acuity at week 52 compared to baseline. Both EYLEA 2Q8 and EYLEA 2Q4 groups were shown to have efficacy that was clinically equivalent to the ranibizumab 0.5 mg Q4 group in year 1.

Detailed results from the analysis of the VIEW1 and VIEW2 studies are shown in Table 5 and Figure 14 below.

Table 5: Efficacy Outcomes at Week 52 (Full Analysis Set with LOCF) in VIEW1 and VIEW2 Studies
 | VIEW1 |  |  | VIEW2
 | EYLEA 2 mg Q8 weeks [After treatment initiation with 3 monthly doses] | EYLEA 2 mg Q4 weeks | ranibizu-mab 0.5 mg Q4 weeks | EYLEA 2 mg Q8 weeks | EYLEA 2 mg Q4 weeks | ranibizu-mab 0.5 mg Q4 weeks
Full Analysis Set | N=301 | N=304 | N=304 | N=306 | N=309 | N=291
Efficacy Outcomes
Proportion of patients who maintained visual acuity (%) (<15 letters of BCVA loss) | 94% | 95% | 94% | 95% | 95% | 95%
Difference [EYLEA group minus the ranibizumab group] (%) (95.1% CI) | 0.6 (-3.2, 4.4) | 1.3 (-2.4, 5.0) |  | 0.6 (-2.9, 4.0) | -0.3 (-4.0, 3.3)
Mean change in BCVA as measured by ETDRS letter score from Baseline | 7.9 | 10.9 | 8.1 | 8.9 | 7.6 | 9.4
Difference in LS mean (95.1% CI) | 0.3 (-2.0, 2.5) | 3.2 (0.9, 5.4) |  | -0.9 (-3.1, 1.3) | -2.0 (-4.1, 0.2)
Number of patients who gained at least 15 letters of vision from Baseline (%) | 92 (31%) | 114 (38%) | 94 (31%) | 96 (31%) | 91 (29%) | 99 (34%)
Difference (%) (95.1% CI) | -0.4 (-7.7, 7.0) | 6.6 (-1.0, 14.1) |  | -2.6 (-10.2, 4.9) | -4.6 (-12.1, 2.9)
BCVA = Best Corrected Visual Acuity; CI = Confidence Interval; ETDRS = Early Treatment Diabetic Retinopathy Study; LOCF = Last Observation Carried Forward (baseline values are not carried forward); 95.1% confidence intervals were presented to adjust for safety assessment conducted during the study

Treatment effects in evaluable subgroups (e.g., age, gender, race, baseline visual acuity) in each study were in general consistent with the results in the overall populations.

Figure 14: Mean Change in Visual Acuity from Baseline to Week 96* in VIEW1 and VIEW2 Studies

*Patient dosing schedules were individualized from weeks 52 to 96 using a modified 12-week dosing regimen.

VIEW1 and VIEW2 studies were both 96 weeks in duration. However, after 52 weeks patients no longer followed a fixed dosing schedule. Between week 52 and week 96, patients continued to receive the drug and dosage strength to which they were initially randomized on a modified 12 week dosing schedule (doses at least every 12 weeks and additional doses as needed). Therefore, during the second year of these studies there was no active control comparison arm.

14.2 Macular Edema Following Central Retinal Vein Occlusion (CRVO)

The safety and efficacy of EYLEA were assessed in two randomized, multi-center, double-masked, sham-controlled studies in patients with macular edema following CRVO. A total of 358 patients were treated and evaluable for efficacy (217 with EYLEA) in the two studies (COPERNICUS and GALILEO). In both studies, patients were randomly assigned in a 3:2 ratio to either 2 mg EYLEA administered every 4 weeks (2Q4), or sham injections (control group) administered every 4 weeks for a total of 6 injections. Protocol-specified visits occurred every 28±7 days. Patient ages ranged from 22 to 89 years with a mean of 64 years.

In both studies, the primary efficacy endpoint was the proportion of patients who gained at least 15 letters in BCVA compared to baseline. At week 24, the EYLEA 2 mg Q4 group was superior to the control group for the primary endpoint.

Results from the analysis of the COPERNICUS and GALILEO studies are shown in Table 6 and Figure 15 below.

Table 6: Efficacy Outcomes at Week 24 (Full Analysis Set with LOCF) in COPERNICUS and GALILEO Studies
 | COPERNICUS |  | GALILEO
 | Control | EYLEA 2 mg Q4 weeks | Control | EYLEA 2 mg Q4 weeks
 | N=73 | N=114 | N=68 | N=103
Efficacy Outcomes
Proportion of patients who gained at least 15 letters in BCVA from Baseline (%) | 12% | 56% | 22% | 60%
Weighted Difference [Difference is EYLEA 2 mg Q4 weeks minus Control] , [Difference and CI are calculated using Cochran-Mantel-Haenszel (CMH) test adjusted for baseline factors; 95.1% confidence intervals were presented to adjust for the multiple assessments conducted during the study] (%) (95.1% CI) |  | 44.8% [p<0.01 compared with Control] (32.9, 56.6) |  | 38.3% (24.4, 52.1)
Mean change in BCVA as measured by ETDRS letter score from Baseline (SD) | -4.0 (18.0) | 17.3 (12.8) | 3.3 (14.1) | 18.0 (12.2)
Difference in LS mean , [LS mean and CI based on an ANCOVA model] (95.1% CI) |  | 21.7 (17.3, 26.1) |  | 14.7 (10.7, 18.7)

Figure 15: Mean Change in BCVA as Measured by ETDRS Letter Score from Baseline to Week 24 in COPERNICUS and GALILEO Studies

Treatment effects in evaluable subgroups (e.g., age, gender, race, baseline visual acuity, retinal perfusion status, and CRVO duration) in each study and in the combined analysis were in general consistent with the results in the overall populations.

14.3 Macular Edema Following Branch Retinal Vein Occlusion (BRVO)

The safety and efficacy of EYLEA were assessed in a 24-week, randomized, multi-center, double-masked, controlled study in patients with macular edema following BRVO. A total of 181 patients were treated and evaluable for efficacy (91 with EYLEA) in the VIBRANT study. In the study, patients were randomly assigned in a 1:1 ratio to either 2 mg EYLEA administered every 4 weeks (2Q4) or laser photocoagulation administered at baseline and subsequently as needed (control group). Protocol-specified visits occurred every 28±7 days. Patient ages ranged from 42 to 94 years with a mean of 65 years.

In the VIBRANT study, the primary efficacy endpoint was the proportion of patients who gained at least 15 letters in BCVA at week 24 compared to baseline. At week 24, the EYLEA 2 mg Q4 group was superior to the control group for the primary endpoint.

Detailed results from the analysis of the VIBRANT study are shown in Table 7 and Figure 16 below.

Table 7: Efficacy Outcomes at Week 24 (Full Analysis Set with LOCF) in VIBRANT Study
 | VIBRANT
 | Control | EYLEA 2 mg Q4 weeks
 | N=90 | N=91
Efficacy Outcomes
Proportion of patients who gained at least 15 letters in BCVA from Baseline (%) | 26.7% | 52.7%
Weighted Difference [Difference is EYLEA 2 mg Q4 weeks minus Control] , [Difference and CI are calculated using Mantel-Haenszel weighting scheme adjusted for region (North America vs. Japan) and baseline BCVA category (> 20/200 and ≤ 20/200)] (%) (95% CI) |  | 26.6% [p<0.01 compared with Control] (13.0, 40.1)
Mean change in BCVA as measured by ETDRS letter score from Baseline (SD) | 6.9 (12.9) | 17.0 (11.9)
Difference in LS mean , [LS mean and CI based on an ANCOVA model] (95% CI) |  | 10.5 (7.1, 14.0)

Figure 16: Mean Change in BCVA as Measured by ETDRS Letter Score from Baseline to Week 24 in VIBRANT Study

Treatment effects in evaluable subgroups (e.g., age, gender, and baseline retinal perfusion status) in the study were in general consistent with the results in the overall populations.

14.4 Diabetic Macular Edema (DME)

The safety and efficacy of EYLEA were assessed in two randomized, multi-center, double-masked, controlled studies in patients with DME. A total of 862 randomized and treated patients were evaluable for efficacy. Protocol-specified visits occurred every 28±7 days. Patient ages ranged from 23 to 87 years with a mean of 63 years.

Of those, 576 were randomized to EYLEA groups in the two studies (VIVID and VISTA). In each study, patients were randomly assigned in a 1:1:1 ratio to 1 of 3 dosing regimens: 1) EYLEA administered 2 mg every 8 weeks following 5 initial monthly injections (EYLEA 2Q8); 2) EYLEA administered 2 mg every 4 weeks (EYLEA 2Q4); and 3) macular laser photocoagulation (at baseline and then as needed). Beginning at week 24, patients meeting a pre-specified threshold of vision loss were eligible to receive additional treatment: patients in the EYLEA groups could receive laser and patients in the laser group could receive EYLEA.

In both studies, the primary efficacy endpoint was the mean change from baseline in BCVA at week 52 as measured by ETDRS letter score. Efficacy of both EYLEA 2Q8 and EYLEA 2Q4 groups was statistically superior to the control group. This statistically superior improvement in BCVA was maintained at week 100 in both studies.

Results from the analysis of the VIVID and VISTA studies are shown in Table 8 and Figure 17 below.

Table 8: Efficacy Outcomes at Weeks 52 and 100 (Full Analysis Set with LOCF) in VIVID and VISTA Studies
 | VIVID |  |  | VISTA
 | EYLEA 2 mg Q8 weeks [After treatment initiation with 5 monthly injections] | EYLEA 2 mg Q4 weeks | Control | EYLEA 2 mg Q8 weeks | EYLEA 2 mg Q4 weeks | Control
Full Analysis Set | N=135 | N=136 | N=132 | N=151 | N=154 | N=154
Efficacy Outcomes at Week 52
Mean change in BCVA as measured by ETDRS letter score from Baseline (SD) | 10.7 (9.3) | 10.5 (9.6) | 1.2 (10.6) | 10.7 (8.2) | 12.5 (9.5) | 0.2 (12.5)
Difference [LS mean and CI based on an ANCOVA model with baseline BCVA measurement as a covariate and a factor for treatment group. Additionally, protocol specified stratification factors were included in the model] , [Difference is EYLEA group minus Control group] in LS mean (97.5% CI) | 9.1 [p<0.01 compared with Control] (6.3, 11.8) | 9.3 (6.5, 12.0) |  | 10.5 (7.7, 13.2) | 12.2 (9.4, 15.0)
Proportion of patients who gained at least 15 letters in BCVA from Baseline (%) | 33.3% | 32.4% | 9.1% | 31.1% | 41.6% | 7.8%
Adjusted Difference, [Difference with confidence interval (CI) and statistical test is calculated using Mantel-Haenszel weighting scheme adjusted by protocol specified stratification factors] (%) (97.5% CI) | 24.2% (13.5, 34.9) | 23.3% (12.6, 33.9) |  | 23.3% (13.5, 33.1) | 34.2% (24.1, 44.4)
Efficacy Outcomes at Week 100
Mean change in BCVA as measured by ETDRS letter score from Baseline (SD) | 9.4 (10.5) | 11.4 (11.2) | 0.7 (11.8) | 11.1 (10.7) | 11.5 (13.8) | 0.9 (13.9)
Difference, in LS mean (97.5% CI) | 8.2 (5.2, 11.3) | 10.7 (7.6, 13.8) |  | 10.1 (7.0, 13.3) | 10.6 (7.1, 14.2)
Proportion of patients who gained at least 15 letters in BCVA from Baseline (%) | 31.1% | 38.2% | 12.1% | 33.1% | 38.3% | 13.0%
Adjusted Difference, (%) (97.5% CI) | 19.0% (8.0, 29.9) | 26.1% (14.8, 37.5) |  | 20.1% (9.6, 30.6) | 25.8% (15.1, 36.6)

Figure 17: Mean Change in BCVA as Measured by ETDRS Letter Score from Baseline to Week 100 in VIVID and VISTA Studies

Treatment effects in the subgroup of patients who had previously been treated with a VEGF inhibitor prior to study participation were similar to those seen in patients who were VEGF inhibitor naïve prior to study participation.

Treatment effects in evaluable subgroups (e.g., age, gender, race, baseline HbA1c, baseline visual acuity, prior anti-VEGF therapy) in each study were in general consistent with the results in the overall populations.

14.5 Diabetic Retinopathy (DR)

Efficacy and safety data of EYLEA in diabetic retinopathy (DR) are derived from the VIVID, VISTA, and PANORAMA studies.

VIVID AND VISTA

In the VIVID and VISTA studies, an efficacy outcome was the change in the Early Treatment Diabetic Retinopathy Study (ETDRS) Diabetic Retinopathy Severity Scale (ETDRS-DRSS). The ETDRS-DRSS score was assessed at baseline and approximately every 6 months thereafter for the duration of the studies [see Clinical Studies (14.4)].

All enrolled patients had DR and DME at baseline. The majority of patients enrolled in these studies (77%) had moderate-to-severe nonproliferative diabetic retinopathy (NPDR) based on the ETDRS-DRSS. At week 100, the proportion of patients improving by at least 2 steps on the ETDRS-DRSS was significantly greater in both EYLEA treatment groups (2Q4 and 2Q8) when compared to the control group.

Results from the analysis of ETDRS-DRSS at week 100 in the VIVID and VISTA studies are shown in Table 9 below.

Table 9: Proportion of Patients Who Achieved a ≥2-Step Improvement from Baseline in the ETDRS-DRSS Score at Week 100 in VIVID and VISTA Studies
 | VIVID |  |  | VISTA
 | EYLEA 2 mg Q8 weeks [After treatment initiation with 5 monthly injections] | EYLEA 2 mg Q4 weeks | Control | EYLEA 2 mg Q8 weeks | EYLEA 2 mg Q4 weeks | Control
Evaluable Patients [The number of evaluable patients included all patients who had valid ETDRS-DRSS data at baseline] | N=101 | N=97 | N=99 | N=148 | N=153 | N=150
Number of patients with a ≥2-step improvement on ETDRS-DRSS from | 32 | 27 | 7 | 56 | 58 | 24
Baseline (%) | (32%) | (28%) | (7%) | (38%) | (38%) | (16%)
Difference [Difference with confidence interval (CI) was calculated using Mantel-Haenszel weighting scheme adjusted by protocol specified stratification factors] , [Difference is EYLEA minus Control group] (%) | 24% [p<0.01 compared with Control] | 21% |  | 22% | 22%
(97.5% CI) | (12, 36) | (9, 33) |  | (11, 33) | (11, 33)
Non-gradable post-baseline ETDRS-DRSS values were treated as missing and were imputed using the last gradable ETDRS-DRSS values (including baseline values if all post-baseline values were missing or non-gradable)

Results of the evaluable subgroups (e.g., age, gender, race, baseline HbA1c, baseline visual acuity) on the proportion of patients who achieved a ≥2-step improvement on the ETDRS-DRSS from baseline to week 100 were, in general, consistent with those in the overall population.

PANORAMA

The PANORAMA study assessed the safety and efficacy of EYLEA in a randomized, multi-center, double-masked, controlled study in patients with moderately severe to severe nonproliferative diabetic retinopathy (NPDR) (ETDRS-DRSS of 47 or 53), without central-involved DME (CI-DME). A total of 402 randomized patients were evaluable for efficacy. Protocol-specified visits occurred every 28±7 days for the first 5 visits, then every 8 weeks (56±7 days). Patient ages ranged from 25 to 85 years with a mean of 55.7 years.

Patients were randomly assigned in a 1:1:1 ratio to 1 of 3 dosing regimens: 1) 3 initial monthly EYLEA 2 mg injections followed by one injection after 8 weeks and then one injection every 16 weeks (EYLEA 2Q16); 2) 5 monthly EYLEA 2 mg injections followed by one injection every 8 weeks (EYLEA 2Q8); and 3) sham treatment.

The primary efficacy endpoint was the proportion of patients who improved by ≥2 steps on the DRSS from baseline to week 24 in the combined EYLEA groups and at week 52 in the 2Q16 and 2Q8 groups individually versus sham. A key secondary endpoint was the proportion of patients developing the composite endpoint of proliferative diabetic retinopathy or anterior segment neovascularization through week 52.

At week 52, efficacy in the 2Q16 and 2Q8 groups was superior to the sham group (see Table 10 and Table 11). The proportion of patients with a ≥2-step improvement over time is shown in Figure 18.

Table 10: Proportion of Patients Who Achieved a ≥2-Step Improvement from Baseline in the ETDRS-DRSS Score at Weeks 24 and 52 in PANORAMA
 | PANORAMA
 | Week 24 |  | Week 52
 | EYLEA Combined | Control (sham) | EYLEA 2Q16 | EYLEA 2Q8 | Control (sham)
Full Analysis Set | N=269 | N=133 | N=135 | N=134 | N=133
Proportion of patients with a ≥2-step improvement on ETDRS-DRSS from Baseline (%) | 58% | 6% | 65% | 80% | 15%
Adjusted Difference [Difference is EYLEA group minus sham] (%) (95% CI) [Difference with CI was calculated using the Mantel-Haenszel weighting scheme adjusted by baseline DRSS stratification variable] | 52% [p<0.01 compared with Control. p-value was calculated using a 2-sided Cochran-Mantel-Haenszel test adjusted by baseline DRSS stratification variable.] (45, 60) |  | 50% (40, 60) | 65% (56, 74)
Non-gradable post-baseline ETDRS-DRSS values were treated as missing and were imputed using the last gradable ETDRS-DRSS values (including baseline values if all post-baseline values were missing or non-gradable)

Figure 18: Proportion of Patients Who Achieved a ≥2-Step Improvement from Baseline in the ETDRS-DRSS Score Through Week 52 in PANORAMA

Table 11: Effect of EYLEA on Worsening of Diabetic Retinopathy in PANORAMA through Week 52
 | EYLEA 2Q16 | EYLEA 2Q8 | Control (Sham)
Full Analysis Set | N=135 | N=134 | N=133
Composite Endpoint of Developing PDR or ASNV [As diagnosed by either the Reading Center or Investigator through week 52]
Event Rate [Estimated using Kaplan-Meier method] | 4.0% [p<0.01 compared with Control] | 2.4% | 20.1%
Hazard Ratio | 0.15 | 0.12
Development of Proliferative Diabetic Retinopathy [Defined as ≥2-step worsening on the ETDRS-DRSS score through week 52]
Event Rate | 1.6% | 0.0% | 11.9%
Hazard Ratio | 0.11 | 0.00
PDR = Proliferative Diabetic Retinopathy; ASNV = Anterior Segment Neovascularization

14.6 Retinopathy of Prematurity (ROP)

Efficacy and safety data of EYLEA in ROP are derived from two studies (BUTTERFLEYE and FIREFLEYE/FIREFLEYE NEXT). BUTTERFLEYE was a 52-week study. FIREFLEYE included 24 weeks of treatment and follow-up. FIREFLEYE NEXT was an observational follow-up of FIREFLEYE through week 52.

Both BUTTERFLEYE and FIREFLEYE studies assessed the efficacy, safety and tolerability of EYLEA in randomized, 2-arm, open-label, parallel-group studies. The studies were conducted in pre-term infants with ROP providing a comparison between EYLEA treatment and laser photocoagulation therapy (laser). Each eligible eye received the assigned study treatment at baseline. Re-treatment and/or rescue treatment was administered if needed based on pre-specified criteria. Rescue treatment could potentially include the alternative treatment (EYLEA or laser). Re-treatment with aflibercept, if required, was administered up to 2 times in a particular eye, with at least 28 days between consecutive injections.

Eligible patients had a maximum gestational age at birth of 32 weeks or a maximum birth weight of 1500 g, had to weigh > 800 g on the day of treatment and had treatment-naïve ROP classified according to the International Classification for Retinopathy of Prematurity (IC-ROP 2005) in at least one eye with one of the following retinal findings:

- ROP Zone 1 Stage 1+, 2+, 3 or 3+, or
- ROP Zone II Stage 2+ or 3+, or
- AP-ROP (aggressive posterior ROP)

The primary efficacy endpoint of each study was the proportion of patients with absence of active ROP and unfavorable structural outcomes (retinal detachment, macular dragging, macular fold, retrolental opacity) at week 52 of chronological age.

In BUTTERFLEYE, patients were randomized in a 3:1 ratio to receive 1 of 2 treatment regimens: 1) EYLEA 0.4 mg at baseline and if required, up to 2 additional injections and 2) laser photocoagulation in each eye at baseline and if required, retreatment. In FIREFLEYE, patients were randomized to the same two treatments, but in a 2:1 ratio. Rescue treatment was administered if required, per pre-specified criteria. In both studies, greater than 92% of all treated patients in the aflibercept group received bilateral injections during the study.

Results from week 52 of chronological age in the BUTTERFLEYE and FIREFLEYE/FIREFLEYE NEXT studies are shown in Table 12 below.

The proportion of patients without clinically significant reactivations of ROP who also did not develop unfavorable structural outcomes was higher in each arm of each study than would have been expected in infants who had not received treatment. Neither trial demonstrated superiority of one arm compared to the other arm. Neither trial demonstrated inferiority of one arm compared to the other arm.

Table 12: Efficacy Outcomes at Week 52 Chronological Age in BUTTERFLEYE and FIREFLEYE/FIREFLEYE NEXT Studies
 | BUTTERFLEYE [In case of bilateral treatment, success was achieved only if both eyes met the primary endpoint. Treatment interval between 2 doses injected into the same eye had to be at least 28 days.] |  | FIREFLEYE/FIREFLEYE NEXT
 | EYLEA 0.4 mg | Laser | EYLEA 0.4 mg | Laser
Full Analysis Set [Included patients who were both randomized and treated from the BUTTERFLEYE and FIREFLEYE/FIREFLEYE NEXT studies. This was the primary analysis population as defined in the Statistical Analysis Plans.]
 | N=93 | N=27 | N=75 | N=38
Efficacy Outcomes
Proportion of patients with absence of active ROP and unfavorable structural outcomes (%) | 79.6% | 77.8% | 78.7% | 81.6%
Adjusted Difference [Difference with confidence interval (CI) was calculated using Mantel-Haenszel weighting scheme adjusted by baseline ROP status. Success criterion: Lower limit of 95.1% CI above -5%.] (%) (95.1% CI) | 1.81% (-15.7, 19.3) |  | -1.88% (-17.0, 13.2)

16 HOW SUPPLIED/STORAGE AND HANDLING

16.1 How Supplied

Each pre-filled syringe or vial is a clear, colorless to pale yellow solution and is for single eye use only. EYLEA is supplied in the following presentations [see Dosage and Administration (2.1), (2.2), (2.3), (2.4) and (2.9)]. Discard unused portion.

NDC NUMBER | CARTON TYPE | CARTON CONTENTS
61755-005-01 | Pre-filled Syringe | one blister pack containing one EYLEA 2 mg (0.05 mL of a 40 mg/mL solution) sterile, single-dose pre-filled glass syringe one Prescribing Information
61755-005-02 | Vial Kit with Injection Components | one EYLEA 2 mg (0.05 mL of a 40 mg/mL solution) single-dose glass vial one 18-gauge × 1½-inch, 5-micron, filter needle for withdrawal of the vial contents one 30-gauge × ½-inch injection needle for intravitreal injection one 1-mL syringe for administration one Prescribing Information

16.2 Storage and Handling

Refrigerate EYLEA at 2°C to 8°C (36°F to 46°F). Do not freeze. Do not use beyond the date stamped on the carton and container label. Store in the original carton until time of use to protect from light. Do not open sealed blister tray until time of use.

17 PATIENT COUNSELING INFORMATION

In the days following EYLEA administration, patients are at risk of developing endophthalmitis, retinal detachment, or retinal vasculitis with or without occlusion. If the eye becomes red, sensitive to light, painful, or develops a change in vision, advise patients and/or caregivers to seek immediate care from an ophthalmologist [see Warnings and Precautions (5.1)].

Patients may experience temporary visual disturbances after an intravitreal injection with EYLEA and the associated eye examinations [see Adverse Reactions (6)]. Advise patients not to drive or use machinery until visual function has recovered sufficiently. In infants with ROP, treatment with EYLEA will necessitate extended periods of ROP monitoring.

Manufactured by:

Regeneron Pharmaceuticals, Inc.

777 Old Saw Mill River Road

Tarrytown, NY 10591-6707

U.S. License Number 1760

For patent information: https://www.regeneron.com/downloads/us-patent-products.pdf

EYLEA is a registered trademark of Regeneron Pharmaceuticals, Inc.

© 2024, Regeneron Pharmaceuticals, Inc.

All rights reserved.

Revised Date: October 2024

PRINCIPAL DISPLAY PANEL - 2 mg/0.05 mL Vial Carton

NDC 61755-005-02

EYLEA®
(aflibercept) Injection
For Intravitreal Injection

2 mg (0.05 mL of a 40 mg/mL solution)
Single-Dose Vial

Carton contents: Each EYLEA carton contains

- one single-dose, 3-mL, glass vial of EYLEA
- one 18-gauge x 1½-inch, 5-micron, filter needle
  for withdrawal of the vial contents (filter needle not
  to be used for intravitreal injection)
- one 30-gauge x ½-inch needle for intravitreal injection
- one 1-mL plastic syringe for administration
- one Prescribing Information

Rx ONLY

PRINCIPAL DISPLAY PANEL - 2 mg/0.05 mL Syringe Carton

NDC 61755-005-01
Rx ONLY

EYLEA®
(aflibercept) Injection
For Intravitreal Injection

2 mg (0.05 mL of a 40 mg/mL solution)

Single-dose Pre-filled Syringe

Carton contents:

- one blister pack containing
  one sterile, single-dose
  pre-filled glass syringe
- one Prescribing Information

REGENERON